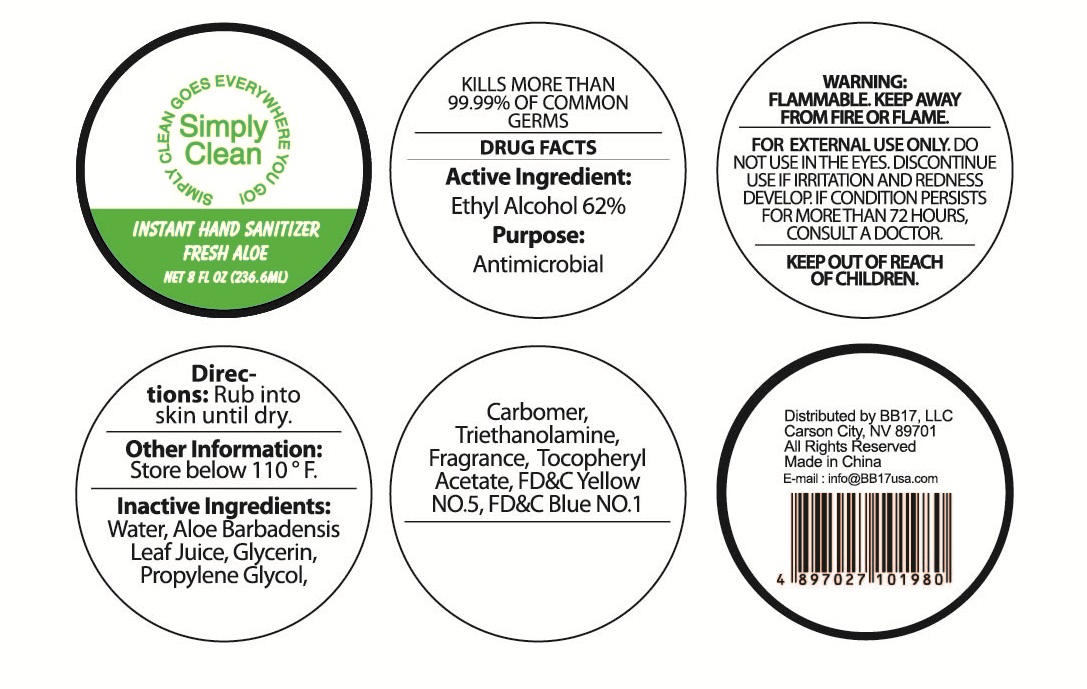 DRUG LABEL: Instant Hand Sanitizer Fresh Aloe
NDC: 53603-2005 | Form: GEL
Manufacturer: BB17, LLC
Category: otc | Type: HUMAN OTC DRUG LABEL
Date: 20130820

ACTIVE INGREDIENTS: Alcohol 62 mL/100 mL
INACTIVE INGREDIENTS: WATER; ALOE; ALOE VERA LEAF; GLYCERIN; PROPYLENE GLYCOL; CARBOMER HOMOPOLYMER TYPE C (ALLYL PENTAERYTHRITOL CROSSLINKED); TROLAMINE; .ALPHA.-TOCOPHEROL ACETATE; FD&C YELLOW NO. 5; FD&C BLUE NO. 1

Active ingredients

Ethyl Alcohol 62% v/v

Purpose
Antimicrobial

INDICATIONS AND USAGE

KILLS MORE THAN 99.99% OF COMMON GERMS

WARNING:

Flammable, Keep away from fire or flame. FOR EXTERNAL USE ONLY. DO NOT USE IN THE EYES.

DISCONTINUE USE IF IRRITATION AND REDNESS DEVELOP.

IF CONDITION PERSISTS FOR MORE THAN 72 HOURS, CONSULT A DOCTOR.

Keep out of reach of children.

DIRECTIONS:

Rub into skin until dry.

Other Information:

Store below 110 F.

INACTIVE INGREDIENTS:Water, Aloe barbadenis, Leaf Juice, Glycerin,

Propylene Glycol, Carbomer, Triethanolamine, Fragrance, Tocopheryl Acetate, FD&C Yellow NO.5, FD&C Blue NO.1